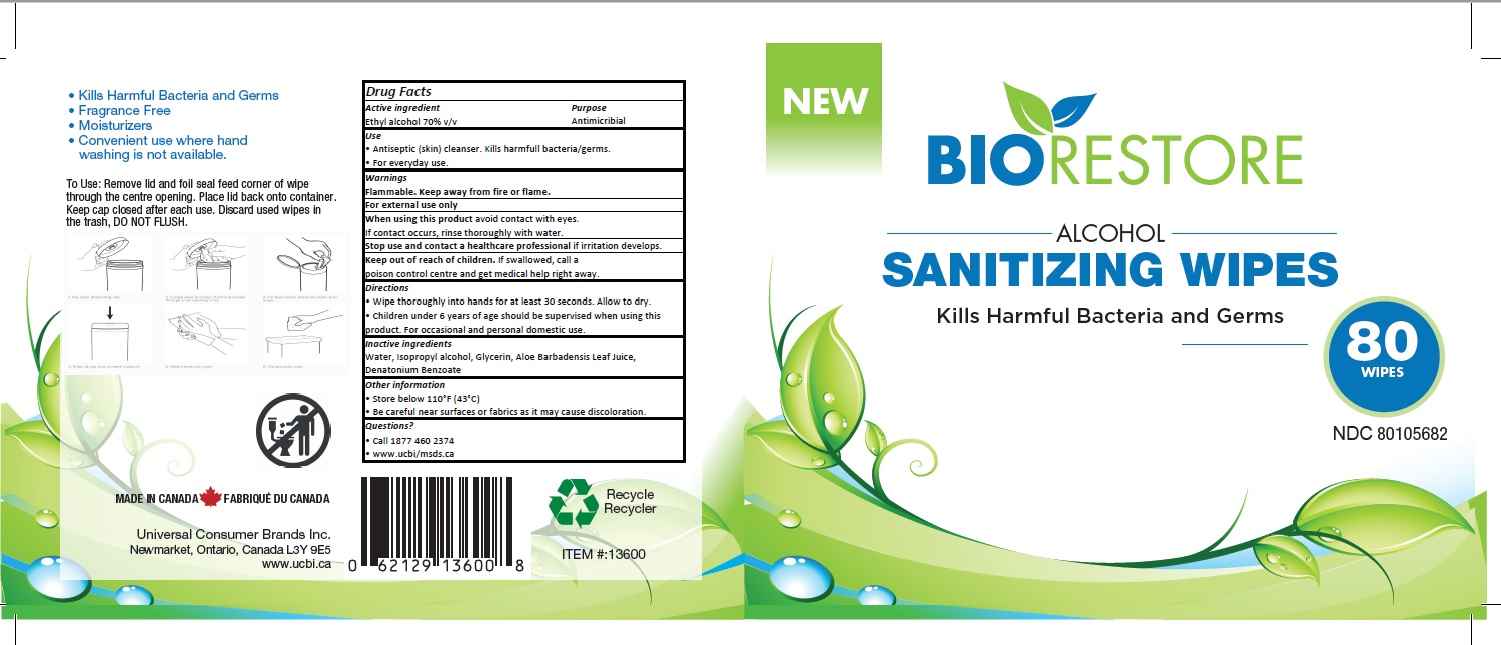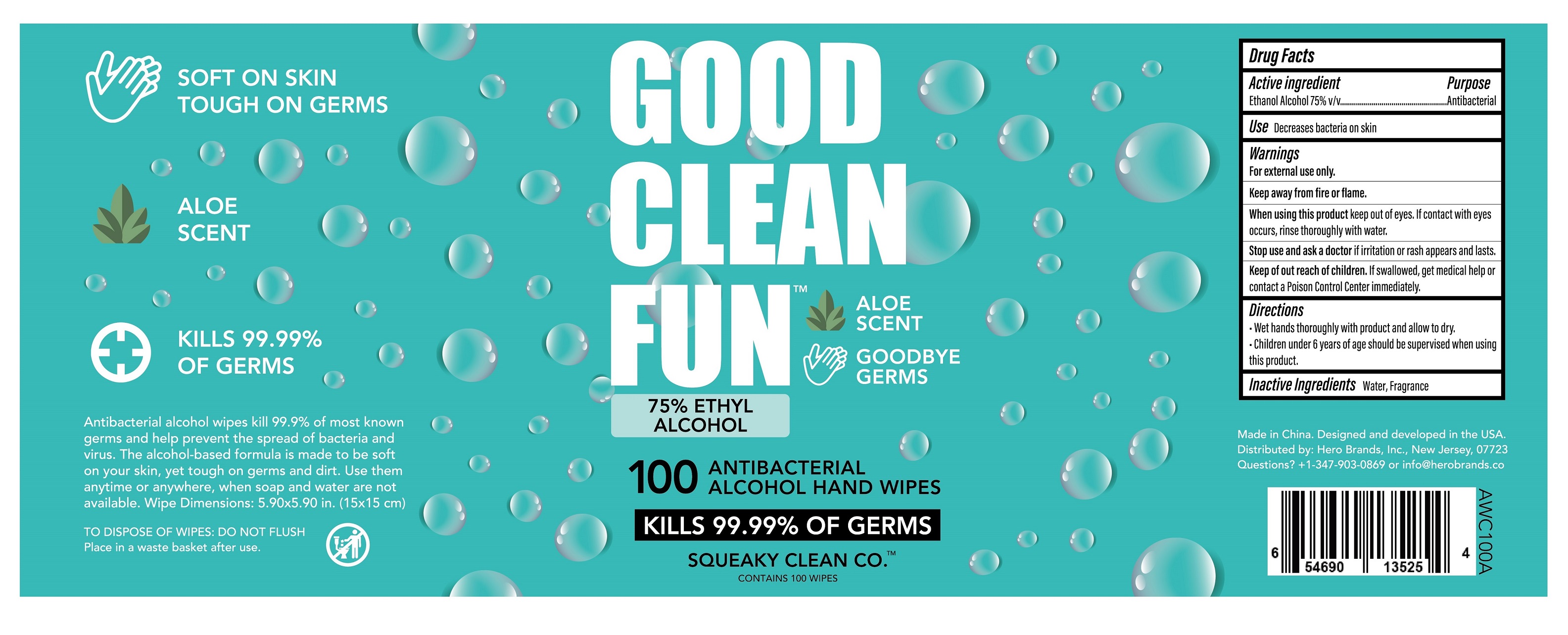 DRUG LABEL: BioRestore Hand Sanitizing Wipes
NDC: 78489-003 | Form: CLOTH
Manufacturer: UNIVERSAL CONSUMER BRANDS INC
Category: otc | Type: HUMAN OTC DRUG LABEL
Date: 20210114

ACTIVE INGREDIENTS: ALCOHOL 70 1/100 1
INACTIVE INGREDIENTS: ALOE; WATER; ISOPROPYL ALCOHOL; DENATONIUM BENZOATE; GLYCERIN

BIORESTORE- Hand Sanitizing wipes

Active Ingredient(s)

Ethanol Alcohol 70% v/v. Purpose: Antimicrobial

Purpose

Antimicrobial

Use

Antiseptic skin cleanser, Kills harmful bacteria

Warnings

- For external use only.
- Keep away from fire or flame

When using

When using this product keep out of eyes. If contact with eyes occurs, rinse thoroughly with water.

Stop use and ask a doctor if irritation or rash appears and lasts.

Keep out of reach of children. If swallowed, get medical help or contact a Poison Control Center immediately.

Directions

- Wipe thoroughly into hands for atleast 30 seconds. Allow to dry.
- Children under 6 years of age should be supervised when using product.

Other information

- Store between 15-30C (59-86F)
- Avoid freezing and excessive heat above 40C (104F)

Inactive ingredients

Water, Fragrance, Isopropyl alcohol, glycerin, denatonium benzoate